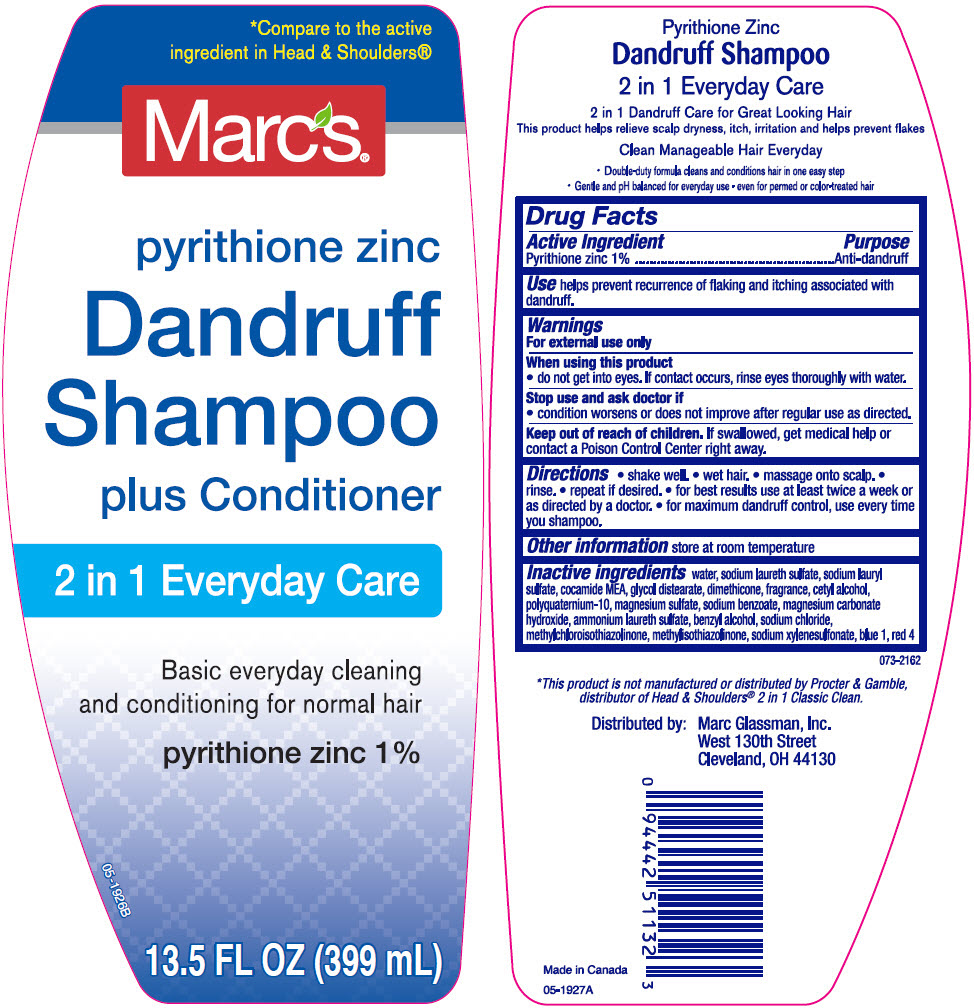 DRUG LABEL: Marcs 2 in 1 Everyday Care Dandruff
NDC: 68998-132 | Form: SHAMPOO
Manufacturer: Mark Glassman, Inc.
Category: otc | Type: HUMAN OTC DRUG LABEL
Date: 20241111

ACTIVE INGREDIENTS: Pyrithione Zinc 10 mg/1 mL
INACTIVE INGREDIENTS: Water; SODIUM LAURETH-3 SULFATE; Sodium Lauryl Sulfate; COCO MONOETHANOLAMIDE; GLYCOL DISTEARATE; Dimethicone; Cetyl Alcohol; POLYQUATERNIUM-10 (30000 MPA.S AT 2%); MAGNESIUM SULFATE, UNSPECIFIED FORM; Sodium Benzoate; Magnesium Carbonate Hydroxide; Benzyl Alcohol; Sodium Chloride; Methylchloroisothiazolinone; Methylisothiazolinone; Sodium Xylenesulfonate; FD&C BLUE NO. 1; FD&C RED NO. 4

Marcs® 2 in1 Everyday Care Dandruff Shampoo & Cond.
Anti-Dandruff

Drug Facts

Active ingredient

Pyrithione Zinc 1%

Purpose

Anti-dandruff

Use

helps prevent recurrence of flaking and itching associated with dandruff.

Warnings

For external use only

When using this product

- do not get into eyes. If contact occurs, rinse eyes thoroughly with water

Stop use and ask a doctor if

- condition worsens or does not improve after regular use of this product as directed

Keep out of reach of children.

If swallowed, get medical help or contact a Poison Control Center right away

Directions

- shake well
- wet hair
- massage onto scalp
- rinse
- repeat if desired
- for best results use at least twice a week or as directed by a doctor
- for maximum dandruff control, use every time you shampoo

Other information

store at room temperature

Inactive ingredients

water, sodium laureth sulfate, sodium lauryl sulfate, cocamide MEA, glycol distearate, dimethicone, fragrance, cetyl alcohol, polyquaternium-10, magnesium sulfate, sodium benzoate, magnesium carbonate hydroxide, ammonium laureth sulfate, benzyl alcohol, sodium chloride, methylchloroisothiazolinone, methylisothiazolinone, sodium xylenesulfonate, blue 1, red 4

Distributed by:
Marc Glassman, Inc.
West 130th Street
Cleveland, OH 44130

PRINCIPAL DISPLAY PANEL - 399 mL Bottle Label

*Compare to the active
ingredient in Head & Shoulders®

Marcs®

pyrithione zinc

Dandruff
Shampoo

plus Conditioner

2 in 1 Everyday Care

Basic everyday cleaning
and conditioning for normal hair

pyrithione zinc 1%

05-1926B

13.5 FL OZ (399 mL)